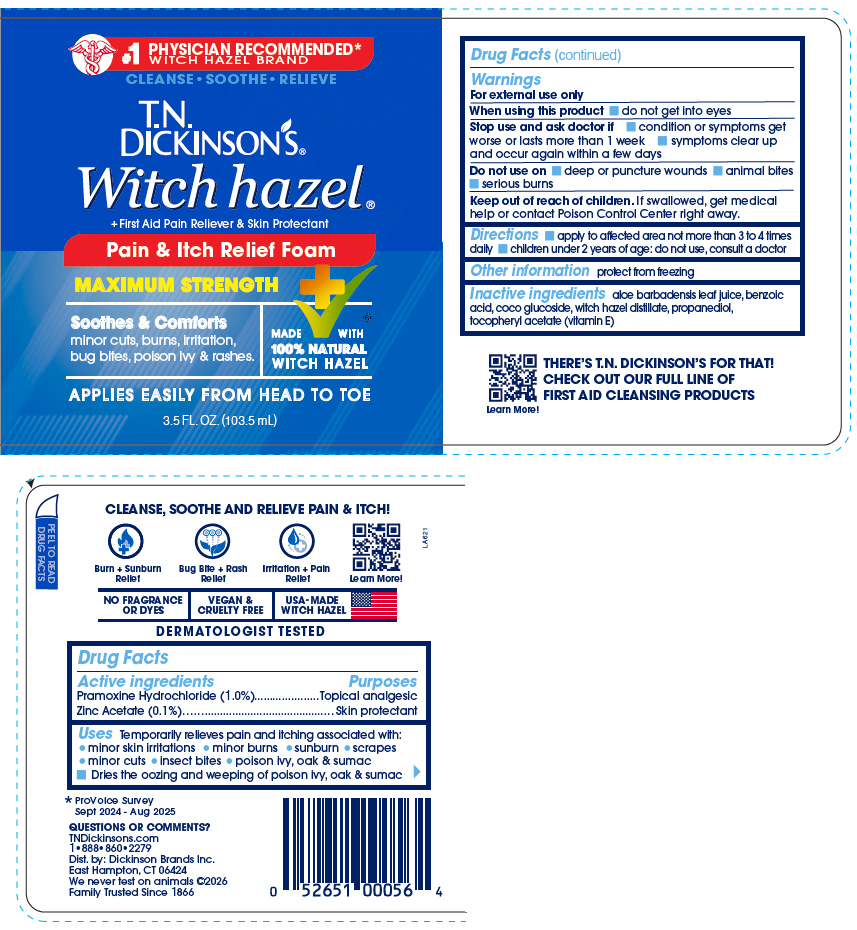 DRUG LABEL: TN Dickinsons Pain and Itch Relief
NDC: 52651-056 | Form: LIQUID
Manufacturer: Dickinson Brands Inc.
Category: otc | Type: HUMAN OTC DRUG LABEL
Date: 20260205

ACTIVE INGREDIENTS: PRAMOXINE HYDROCHLORIDE 0.01 g/1 mL; ZINC ACETATE 0.001 g/1 mL
INACTIVE INGREDIENTS: HAMAMELIS VIRGINIANA TOP WATER; BENZOIC ACID; PROPANEDIOL; ALOE VERA LEAF JUICE; COCO-GLUCOSIDE; .ALPHA.-TOCOPHEROL ACETATE, DL-

T.N. Dickinson's® Pain and Itch Relief

Drug Facts

ACTIVE INGREDIENT

PURPOSE

Active ingredients | Purposes
Pramoxine Hydrochloride (1.0%) | Topical analgesic
Zinc Acetate (0.1%) | Skin protectant

Uses

Temporarily relieves pain and itching associated with:

- minor skin irritations
- minor burns
- sunburn
- scrapes
- minor cuts
- insect bites
- poison ivy, oak & sumac
  - Dries the oozing and weeping of poison ivy, oak & sumac

Warnings

For external use only

When using this product

- do not get into eyes

Stop use and ask doctor if

- condition or symptoms get worse or lasts more than 1 week
- symptoms clear up and occur again within a few days

Do not use on

- deep or puncture wounds
- animal bites
- serious burns

Keep out of reach of children. If swallowed, get medical help or contact Poison Control Center right away.

Directions

- apply to affected area not more than 3 to 4 times daily
- children under 2 years of age: do not use, consult a doctor

Other information

protect from freezing

Inactive ingredients

aloe barbadensis leaf juice, benzoic acid, coco glucoside, witch hazel distillate, propanediol, tocopheryl acetate (vitamin E)

QUESTIONS OR COMMENTS?

TNDickinsons.com
1•888•860•2279

Dist. by: Dickinson Brands Inc.
East Hampton, CT 06424

PRINCIPAL DISPLAY PANEL - 103.5 mL Bottle Label

#1 PHYSICIAN RECOMMENDED*
WITCH HAZEL BRAND

CLEANSE • SOOTHE • RELIEVE

T.N.
DICKINSON'S®

Witch hazel®
+First Aid Pain Reliever & Skin Protectant

Pain & Itch Relief Foam

MAXIMUM STRENGTH

Soothes & Comforts
minor cuts, burns, irritation,
bug bites, poison ivy & rashes.

MADE WITH
100% NATURAL
WITCH HAZEL

APPLIES EASILY FROM HEAD TO TOE

3.5 FL. OZ. (103.5 mL)